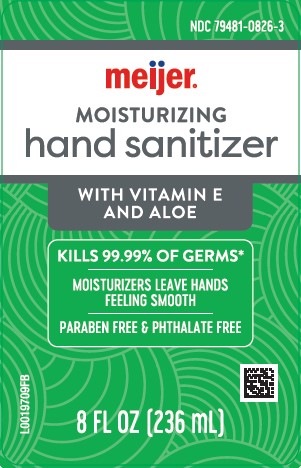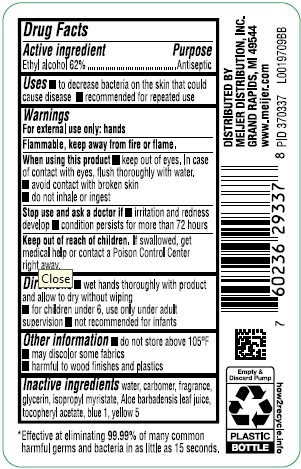 DRUG LABEL: Alcohol
NDC: 79481-0826 | Form: LIQUID
Manufacturer: Meijer, Inc.
Category: otc | Type: HUMAN OTC DRUG LABEL
Date: 20260219

ACTIVE INGREDIENTS: ALCOHOL 62 mL/100 mL
INACTIVE INGREDIENTS: CARBOMER INTERPOLYMER TYPE A (ALLYL SUCROSE CROSSLINKED); GLYCERIN; TOCOPHEROL; WATER; ISOPROPYL MYRISTATE; ALOE; FD&C BLUE NO. 1; FD&C YELLOW NO. 5

Meijer 826.000/826AA rev 1
Moisturizing Hand Sanitizer with Aloe

Active ingredient

Ethyl Alcohol 62%

Purpose

Antiseptic

Uses

- to decrease bacteria on the skin that could cause disease
- recommended for repeated use

Warnings

For external use only: hands

Flammable, keep away from fire or flame.

When using this product

- keep out of eyes. In case of contact with eyues, flush thoroughly with water
- aoid contact with broken skin
- do not inhale of ingest

Stop use and ask a doctor if

- irritation and redness develop
- condition persists for more than 72 hours

Keep out of reach of children.

If swallowed, get medical help or contact a Poison Control Center right away.

Directions

- wet hands thoroughly with product and allow to dry without wiping
- for children under 6, use only under adult supervision
- not recommended for infants

Other information

- Do not store above 105°F
- may discolor some fabrics
- harmful to wood finishes and plastics

Inactive ingredients

water, carbomer, fragrance, glycerin, isopropyl myristate, Aloe barbadensis leaf juice, tocopheryl acetate, blue 1, yellow 5

Disclaimer

*Effective at eliminating 99.99% of many common harmful germs and bacteria in as little as 15 seconds.

Adverse Reaction

DISTRIBUTED BY

MEIJER DISTRIBUTION, INC.

GRAND RAPIDS, MI 49544

www.meijer.com

Empty & Discard Pump

PLASTIC BOTTLE

how2recycle.info

Principal display panel

NDC 79481-0826-3

meijer®

MOISTURIZING

hand sanitizer

WITH VITAMIN E AND ALOE

KILLS 99.99% OF GERMS*

MOISTURIZERS LEAVE HANDS FEELING SMOOTH

PARABEN FREE & PHTHALATE FREE

8 FL OZ (236 mL)